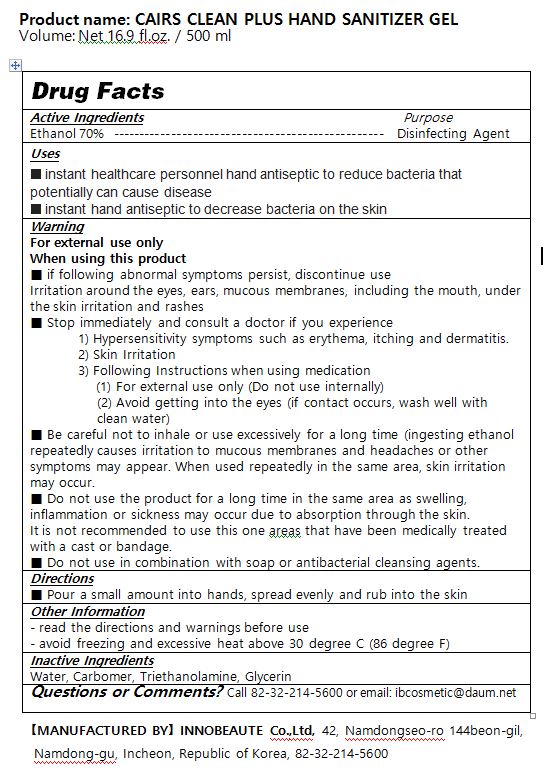 DRUG LABEL: CAIRS CLEAN PLUS HAND SANITIZER gel
NDC: 79233-0001 | Form: GEL
Manufacturer: INNOBEAUTE Co.,Ltd
Category: otc | Type: HUMAN OTC DRUG LABEL
Date: 20200714

ACTIVE INGREDIENTS: ALCOHOL 70 mL/100 mL
INACTIVE INGREDIENTS: WATER; CARBOMER HOMOPOLYMER, UNSPECIFIED TYPE; TROLAMINE; GLYCERIN

ACTIVE INGREDIENT

alcohol

PURPOSE

Antiseptic

INDICATIONS AND USAGE

■ instant healthcare personnel hand antiseptic to reduce bacteria that potentially can cause disease

■ instant hand antiseptic to decrease bacteria on the skin

WARNINGS

For external use only

When using this product

■ if following abnormal symptoms persist, discontinue use

Irritation around the eyes, ears, mucous membranes, including the mouth, under the skin irritation and rashes

■ Stop immediately and consult a doctor if you experience

1) Hypersensitivity symptoms such as erythema, itching and dermatitis.

2) Skin Irritation

3) Following Instructions when using medication

(1) For external use only (Do not use internally)

(2) Avoid getting into the eyes (if contact occurs, wash well with clean water)

■ Be careful not to inhale or use excessively for a long time (ingesting ethanol repeatedly causes irritation to mucous membranes and headaches or other symptoms may appear. When used repeatedly in the same area, skin irritation may occur.

■ Do not use the product for a long time in the same area as swelling, inflammation or sickness may occur due to absorption through the skin.

It is not recommended to use this one areas that have been medically treated with a cast or bandage.

■ Do not use in combination with soap or antibacterial cleansing agents.

DOSAGE AND ADMINISTRATION

for external use only

INACTIVE INGREDIENT

Water, Carbomer, Triethanolamine, Glycerin

Keep out of reach of children